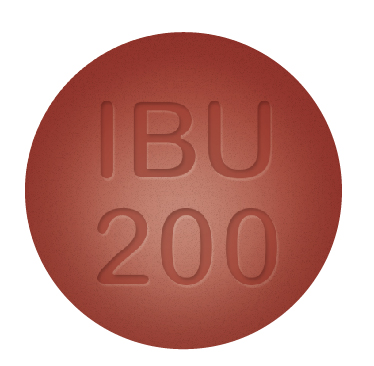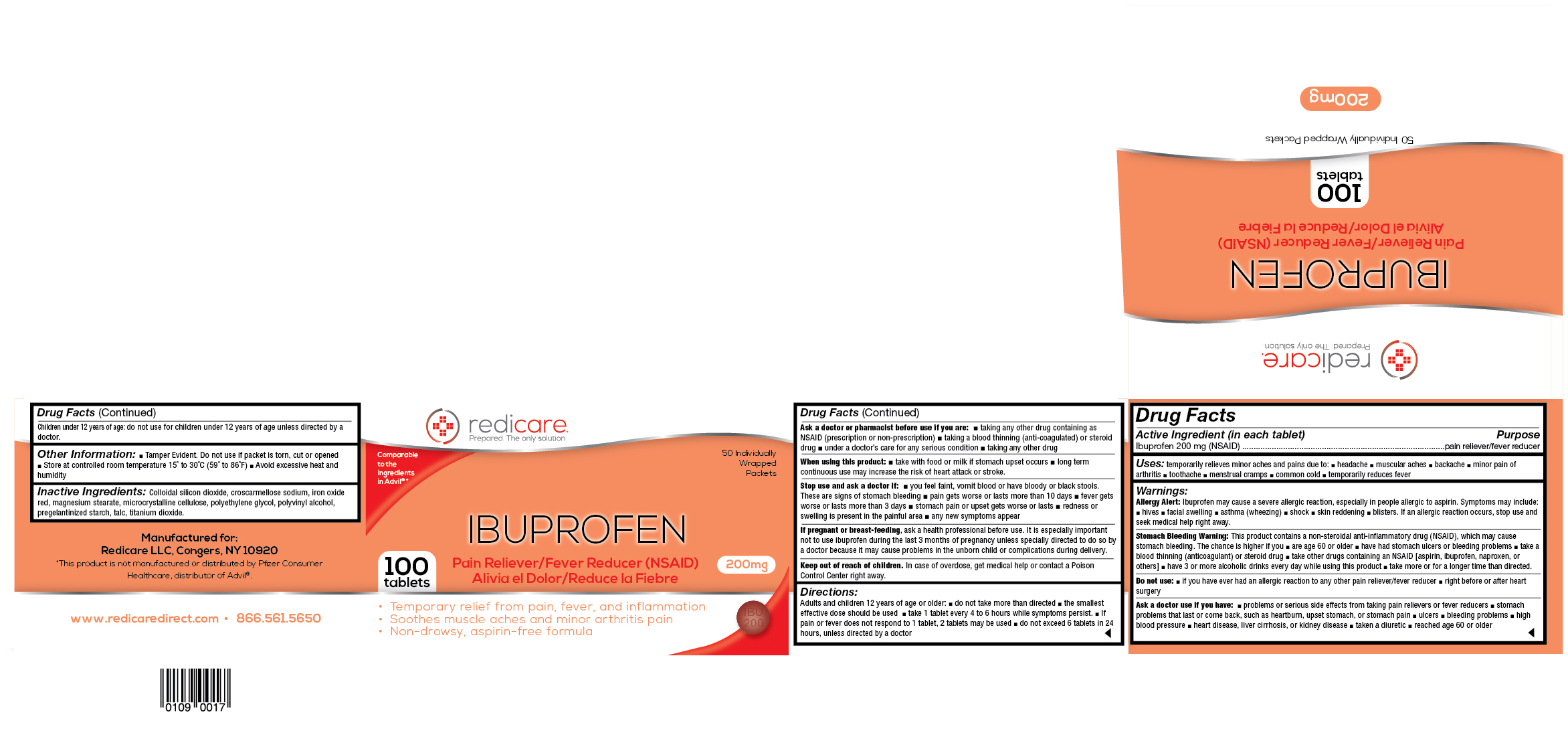 DRUG LABEL: Redicare Ibuprofen
NDC: 71105-750 | Form: TABLET, FILM COATED
Manufacturer: Redicare LLC
Category: otc | Type: HUMAN OTC DRUG LABEL
Date: 20210702

ACTIVE INGREDIENTS: IBUPROFEN 200 1/200 1
INACTIVE INGREDIENTS: FERRIC OXIDE RED; POLYETHYLENE GLYCOL 400; POLYVINYL ALCOHOL, UNSPECIFIED; STARCH, PREGELATINIZED CORN; TALC; TITANIUM DIOXIDE; MAGNESIUM STEARATE; CELLULOSE, MICROCRYSTALLINE; SILICON DIOXIDE; CROSCARMELLOSE SODIUM

Ibuprofen 200mg

Active Ingredient (in each tablet) Purpose

Ibuprofen 200 mg (NSAID) .........................................................................................pain reliever/fever reducer

Uses

temporarily relieves minor aches and pains due to: ■ headache ■ muscular aches ■ backache ■ minor pain of arthritis ■ toothache ■ menstrual cramps ■ common cold ■ temporarily reduces fever

Warnings

Allergy Alert: Ibuprofen may cause a severe allergic reaction, especially in people allergic to aspirin. Symptoms may include: ■ hives ■ facial swelling ■ asthma (wheezing) ■ shock ■ skin reddening ■ blisters. If an allergic reaction occurs, stop use and seek medical help right away.
Stomach Bleeding Warning: This product contains a non-steroidal anti-inflammatory drug (NSAID), which may cause stomach bleeding. The chance is higher if you ■ are age 60 or older ■ have had stomach ulcers or bleeding problems ■ take a blood thinning (anticoagulant) or steroid drug ■ take other drugs containing an NSAID [aspirin, ibuprofen, naproxen, or others] ■ have 3 or more alcoholic drinks every day while using this product ■ take more or for a longer time than directed.

Do not use

■ if you have ever had an allergic reaction to any other pain reliever/fever reducer ■ right before or after heart surgery

Ask a doctor use if you have:

■ problems or serious side effects from taking pain relievers or fever reducers ■ stomach problems that last or come back, such as heartburn, upset stomach, or stomach pain ■ ulcers ■ bleeding problems ■ high blood pressure ■ heart disease, liver cirrhosis, or kidney disease ■ taken a diuretic ■ reached age 60 or older

Ask a doctor or pharmacist before use if you are:

■ taking any other drug containing as NSAID (prescription or non-prescription) ■ taking a blood thinning (anti-coagulated) or steroid drug ■ under a doctor’s care for any serious condition ■ taking any other drug

When using this product:

■ take with food or milk if stomach upset occurs ■ long term continuous use may increase the risk of heart attack or stroke.

Stop use and ask a doctor if:

■ you feel faint, vomit blood or have bloody or black stools. These are signs of stomach bleeding ■ pain gets worse or lasts more than 10 days ■ fever gets worse or lasts more than 3 days ■ stomach pain or upset gets worse or lasts ■ redness or swelling is present in the painful area ■ any new symptoms appear

If pregnant or breast-feeding,

ask a health professional before use. It is especially important not to use ibuprofen during the last 3 months of pregnancy unless specially directed to do so by a doctor because it may cause problems in the unborn child or complications during delivery.

Keep out of reach of children.

In case of overdose, get medical help or contact a Poison Control Center right away.

Directions

Adults and children 12 years and older do not take more than directed - the smallest effective dose should be used - take 1 tablet every 4 to 6 hours while symptoms persist - If pain or fever does not respond to 1 tablet take a 2nd tablet - do not exceed 6 tablets in 24 hours unless directed by a doctor

Children under 12 years of age do not use unless directed by a doctor

Other Information:

■ Tamper Evident. Do not use if packet is torn, cut or opened ■ Store at controlled room temperature 15˚ to 30˚C (59˚ to 86˚F) ■ Avoid excessive heat and humidity

Inactive Ingredients:

Colloidal silicon dioxide, croscarmellose sodium, iron oxide red, magnesium stearate, microcrystalline cellulose, polyethylene glycol, polyvinyl alcohol, pregelantinized starch, talc, titanium dioxide.